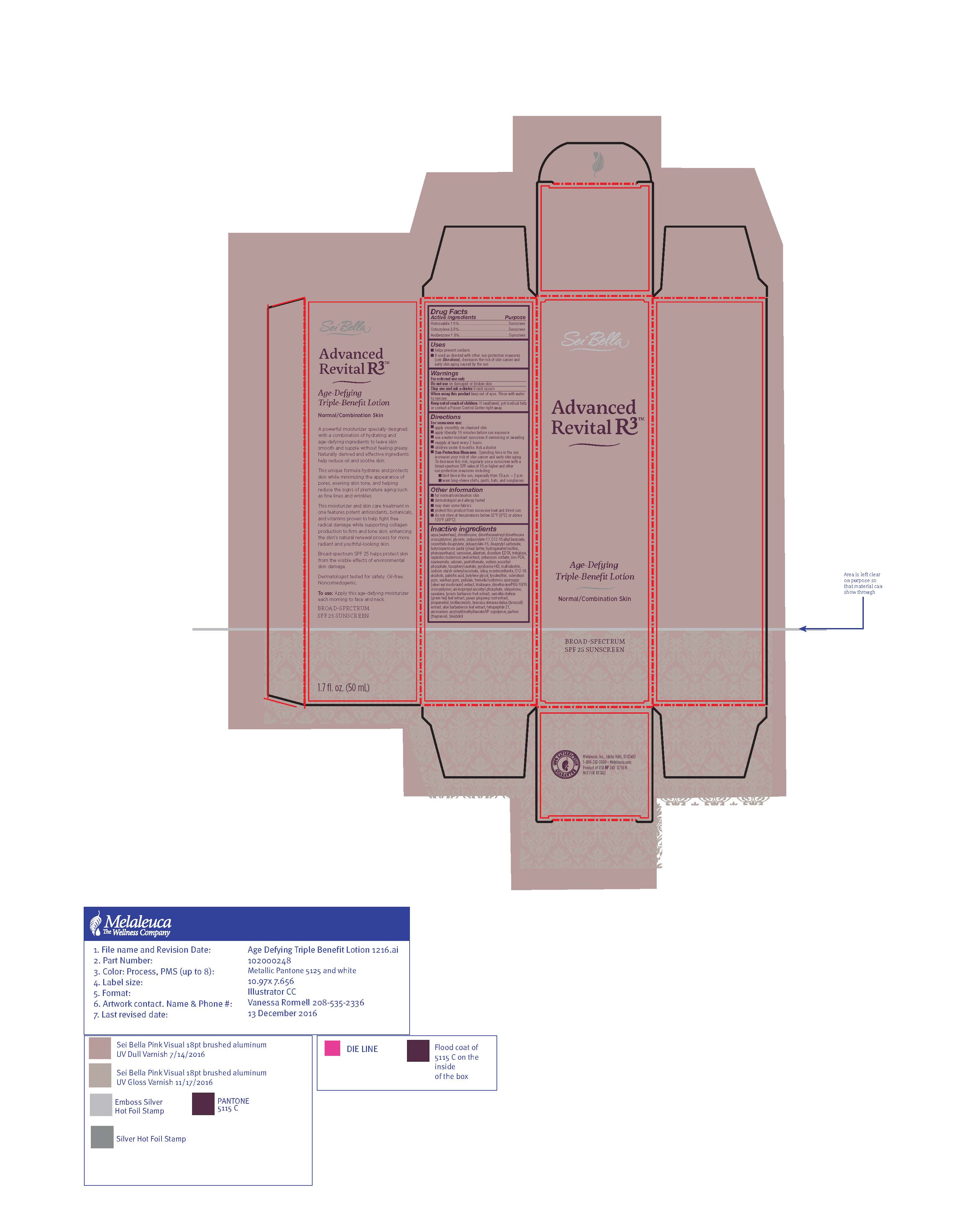 DRUG LABEL: Advanced Revital
NDC: 54473-277 | Form: LOTION
Manufacturer: Melaleuca, Inc.
Category: otc | Type: HUMAN OTC DRUG LABEL
Date: 20200319

ACTIVE INGREDIENTS: AVOBENZONE 0.9 g/50 mL; HOMOSALATE 3 g/50 mL; OCTOCRYLENE 0.93 g/50 mL
INACTIVE INGREDIENTS: SILICON DIOXIDE; CARNOSINE; BETASIZOFIRAN; ZINC PIDOLATE; SAPINDUS MUKOROSSI FRUIT RIND; NIACINAMIDE; CALCIUM PANTOTHENATE; TREMELLA FUCIFORMIS FRUITING BODY; UBIDECARENONE; ALPHA-TOCOPHEROL ACETATE; LEVOMENOL; POTASSIUM SORBATE; TETRAPEPTIDE-21; ALLANTOIN; ALOE VERA LEAF; ASIAN GINSENG; BUTYLENE GLYCOL; ALKYL (C12-15) BENZOATE; DIMETHICONE/VINYL DIMETHICONE CROSSPOLYMER (SOFT PARTICLE); ISOSORBIDE DICAPRYLATE; DICAPRYLYL CARBONATE; LECITHIN, SOYBEAN; CAMELLIA OLEIFERA LEAF; AMMONIUM ACRYLOYLDIMETHYLTAURATE/VP COPOLYMER; AMINOPROPYL ASCORBYL PHOSPHATE; C12-16 ALCOHOLS; PALMITIC ACID; TREHALOSE; DIMETHICONE; GLYCERIN; SQUALANE; LYCIUM BARBARUM FRUIT; PHENOXYETHANOL; EDETATE DISODIUM ANHYDROUS; SHEA BUTTER; TRISILOXANE; MALTODEXTRIN; PROPANEDIOL; WATER; XANTHAN GUM; PULLULAN; MONTMORILLONITE; SODIUM ASCORBYL PHOSPHATE; PYRIDOXINE HYDROCHLORIDE; CITRUS BIOFLAVONOIDS; BROCCOLI SPROUT

Sei Bella Advanced Revital R3 Age Defying Lotion SPF 25 Normal to Oily

Active ingredients
Avobenzone 1.8%, Homosalate 6%, Octisalate 3%, Octocrylene 1.86%, Oxybenzone 1.8%

Purpose
Sunscreen

Use

- provides moderate protection against sunburn

Warnings
For external use only

When using this product

- keep out of eyes. Rinse with water to remove.

Stop use and ask a doctor if

- rash or irritation develops and lasts

Keep out of reach of children. If swallowed, get medical help or contact a Poison Control Center right away.

Directions

- apply smoothly on cleansed skin before sun exposure and as needed
- children under six months of age: ask a doctor

Other information

- dermatologist and allergy tested

GENERAL PRECAUTIONS

- Sun alert: Limiting sun exposure, wearing protective clothing, and using sunscreens may reduce the risks of skin aging, skin cancer, and other harmful effects of the sun
- may stain some fabrics

STORAGE AND HANDLING

- do not store at temperatures below 32°F (0°C) or above 120°F (49°C)

Inactive ingredients
aqua (water/eau), polyacrylate-15, polyacrylate-17, C20-22 alkyl phosphate, C20-22 alcohols, trisiloxane, dimethicone, cyclopentasiloxane, dimethicone crosspolymer, cetyl palmitate, glycerin, butyrospermum parkii (shea butter), C12-15 alkyl benzoate, dicaprylyl carbonate, C14-22 alcohols, C12-20 alkyl glucoside, propylheptyl caprylate, acetyl tetrapeptide-9, phenoxyethanol, cetyl alcohol, caprylyl glycol, 1,2 hexanediol, triethanolamine, xanthan gum, trisodium ethylenediamine disuccinate, parfum, bisabolol, panax ginseng root extract, lycium barbarum fruit extract, aloe barbadensis leaf juice, camellia oleifera leaf extract, butylene glycol, allantoin, tocopheryl acetate, limonene, butylphenyl methylpropional